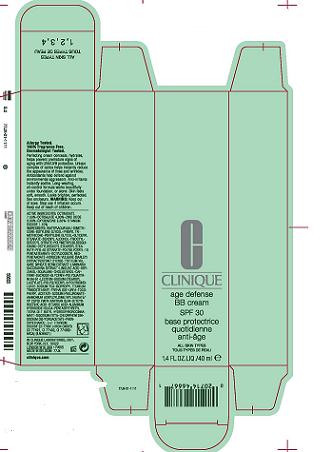 DRUG LABEL: Age Defense BB Cream
NDC: 49527-760 | Form: CREAM
Manufacturer: CLINIQUE LABORATORIES INC
Category: otc | Type: HUMAN OTC DRUG LABEL
Date: 20100623

ACTIVE INGREDIENTS: OCTINOXATE 7.5 mL/100 mL; OCTISALATE 4.0 mL/100 mL; ZINC OXIDE 3.5 mL/100 mL; OXYBENZONE 2.5 mL/100 mL; TITANIUM DIOXIDE 1.1 mL/100 mL

ACTIVE INGREDIENT

OCTINOXATE 7.5%, OCTISALATE 4.0%, ZINC OXIDE 3.5%, OXYBENZONE 2.5%, TITANIUM DIOXIDE 1.1%

WHEN USING

Apply daily all over face.

WARNINGS

Keep out of eyes. Stop use if irritation occurs. Keep out of reach of children.

PACKAGE LABEL

PRINCIPAL DISPLAY PANEL:

Clinique

Age Defense BB Cream

SPF 30

40ml 1.4Floz

Clinique Laboratories, Dist.

New York, NY 10022
77jxcarton.jpg